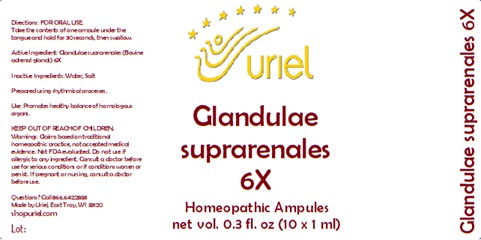 DRUG LABEL: Glandulae suprarenales 6
NDC: 48951-5021 | Form: LIQUID
Manufacturer: Uriel Pharmacy Inc.
Category: homeopathic | Type: HUMAN OTC DRUG LABEL
Date: 20241205

ACTIVE INGREDIENTS: BOS TAURUS ADRENAL GLAND 6 [hp_X]/1 mL
INACTIVE INGREDIENTS: WATER; SODIUM CHLORIDE

Glandulae suprarenales 6

INDICATIONS AND USAGE

Directions: FOR ORAL USE.

DOSAGE AND ADMINISTRATION

Take the contents of one ampule under the tongue and hold for 30 seconds, then swallow.

Active Ingredient: Glandulae
suprarenales (Bovine adrenal glands) 6X

Inactive Ingredients: Water, Salt

Prepared using rhythmical processes.

PURPOSE

Use: Promotes healthy balance of homologous organs.

KEEP OUT OF REACH OF CHILDREN.

WARNINGS

Warnings: Claims based on traditional homeopathic practice, not accepted medical evidence. Not FDA evaluated. Do not use if allergic to any ingredient. Consult a doctor before use for serious conditions or if conditions worsen or persist. If pregnant or nursing, consult a doctor before use.

QUESTIONS

Questions? Call 866.642.2858 Uriel, East Troy, WI 53120 shopuriel.com Lot: